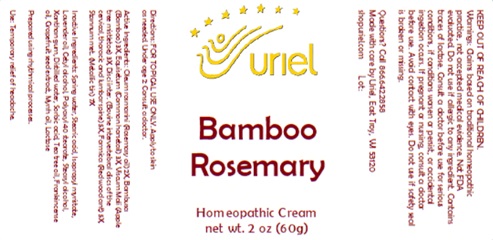 DRUG LABEL: Bamboo Rosemary
NDC: 48951-2130 | Form: CREAM
Manufacturer: Uriel Pharmacy Inc.
Category: homeopathic | Type: HUMAN OTC DRUG LABEL
Date: 20241114

ACTIVE INGREDIENTS: FORMICA RUFA 5 [hp_X]/1 g; ROSEMARY OIL 2 [hp_X]/1 g; EQUISETUM ARVENSE TOP 3 [hp_X]/1 g; VISCUM ALBUM FRUITING TOP 3 [hp_X]/1 g; BAMBUSA VULGARIS WHOLE 3 [hp_X]/1 g; TIN 7 [hp_X]/1 g; BOS TAURUS INTERVERTEBRAL DISC 5 [hp_X]/1 g
INACTIVE INGREDIENTS: SORBIC ACID; LACTOSE, UNSPECIFIED FORM; WATER; CETYL ALCOHOL; FRANKINCENSE OIL; TEA TREE OIL; LAVENDER OIL; CITRUS PARADISI SEED; STEARIC ACID; ISOPROPYL MYRISTATE; POLYOXYL 40 STEARATE; STEARYL ALCOHOL; MYRRH OIL; XANTHAN GUM

Bamboo Rosemary

INDICATIONS AND USAGE

Directions: FOR TOPICAL USE ONLY.

DOSAGE AND ADMINISTRATION

Apply to skin as needed. Under age 2: Consult a doctor.

ACTIVE INGREDIENT

Active Ingredients: Oleum rosmarini (Rosemary oil) 2X, Bambusa (Bamboo) 3X, Equisetum (Common horsetail) 3X, Viscum Mali (Apple tree mistletoe) 3X, Disci inter. (Bovine intervertebral discs of the cervical, thoracic and lumbar spine) 5X, Formica (Red wood ant) 5X, Stannum met. (Metallic tin) 7X

INACTIVE INGREDIENT

Inactive Ingredients: Spring water, Stearic acid, Isopropyl myristate, Lavender oil, Cetyl alcohol, Polyoxyl 40 stearate, Stearyl alcohol, Xanthan gum, Distilled water, Sorbic acid, Tea tree oil, Frankincense oil, Grapefruit seed extract, Myrrh oil, Lactose

Prepared using rhythmical processes.

PURPOSE

Use: Temporary relief of headache.

KEEP OUT OF REACH OF CHILDREN.

Warnings: FOR EXTERNAL USE ONLY.
Claims based on traditional homeopathic practice, not accepted medical evidence. Not FDA evaluated. Do not use if allergic to any ingredient. Contains traces of lactose. Consult a doctor before use for serious conditions, if conditions worsen or persist, or accidental ingestion occurs. If pregnant or nursing, consult a doctor before use. Avoid
contact with eyes. Do not use if safety seal is broken or missing.

Questions? Call 866.642.2858
Made with care by Uriel, East Troy, WI 53120
shopuriel.com Lot: